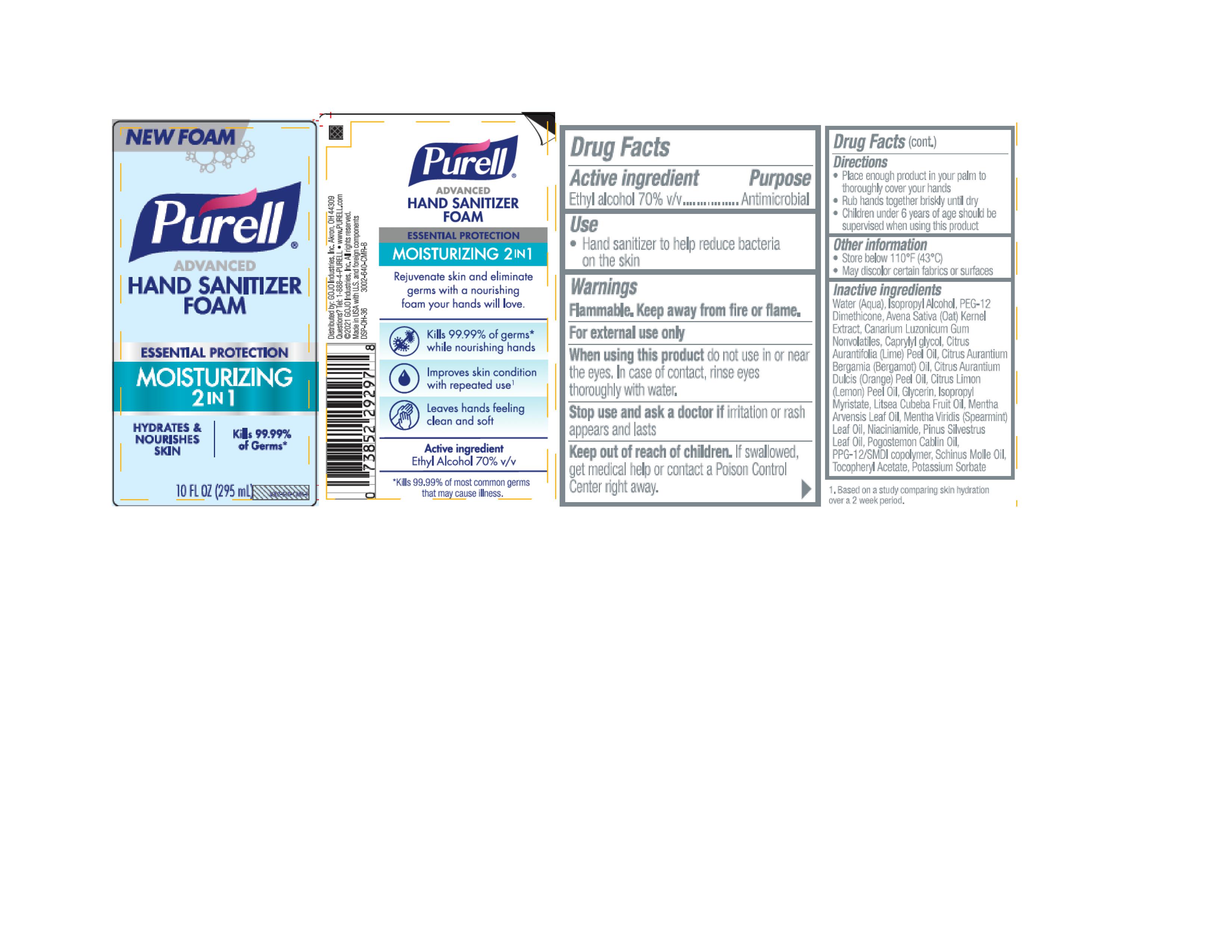 DRUG LABEL: PURELL Advanced Hand Sanitizer Moisturizing 2in1 Foam
NDC: 21749-851 | Form: LIQUID
Manufacturer: GOJO Industries, Inc.
Category: otc | Type: HUMAN OTC DRUG LABEL
Date: 20241216

ACTIVE INGREDIENTS: ALCOHOL 70 mL/100 mL
INACTIVE INGREDIENTS: WATER; ISOPROPYL ALCOHOL; PEG-12 DIMETHICONE (300 CST); OAT; ELEMI; CAPRYLYL GLYCOL; LIME OIL; BERGAMOT OIL; ORANGE OIL; LEMON OIL; GLYCERIN; ISOPROPYL MYRISTATE; LITSEA OIL; MENTHA ARVENSIS LEAF OIL; SPEARMINT OIL; NIACINAMIDE; PINE NEEDLE OIL (PINUS SYLVESTRIS); PATCHOULI OIL; PPG-12/SMDI COPOLYMER; SCHINUS MOLLE FRUIT OIL; .ALPHA.-TOCOPHEROL ACETATE; POTASSIUM SORBATE

PURELL® Advanced Hand Sanitizer Moisturizing 2in1 Foam

Active ingredient

Ethyl Alcohol 70% v/v

Purpose

Antimicrobial

Use

• Hand sanitizer to help reduce bacteria on the skin

Warnings

Flammable. Keep away from fire or flame.

For external use only.

WHEN USING

When using this productdo not use in or near the eyes. In case of contact, rinse eyes thoroughly with water.

Stop use and ask a doctor ifirritation or rash appears and lasts.

Keep out of reach of children.If swallowed, get medical help or contact a Poison Control Center right away.

Directions

• Place enough product in your palm to thoroughly cover your hands

• Rub hands together briskly until dry

• Children under 6 years of age should be supervised when using this product

Inactive ingredients

Water (Aqua), Isopropyl Alcohol, PEG-12 Dimethicone, Avena Sativa (Oat) Kernel Extract, Canarium Luzonicum Gum Nonvolatiles, Caprylyl glycol, Citrus Aurantifolia (Lime) Peel Oil, Citrus Aurantium Bergamia (Bergamot) Oil, Citrus Aurantium Dulcis (Orange) Peel Oil, Citrus Limon (Lemon) Peel Oil, Glycerin, Isopropyl Myristate, Litsea Cubeba Fruit Oil, Mentha Arvensis Leaf Oil, Mentha Viridis (Spearmint) Leaf Oil, Niaciniamide, Pinus Silvestrus Leaf Oil, Pogostemon Cablin Oil, PPG-12/SMDI copolymer, Schinus Molle Oil, Tocopheryl Acetate, Potassium Sorbate